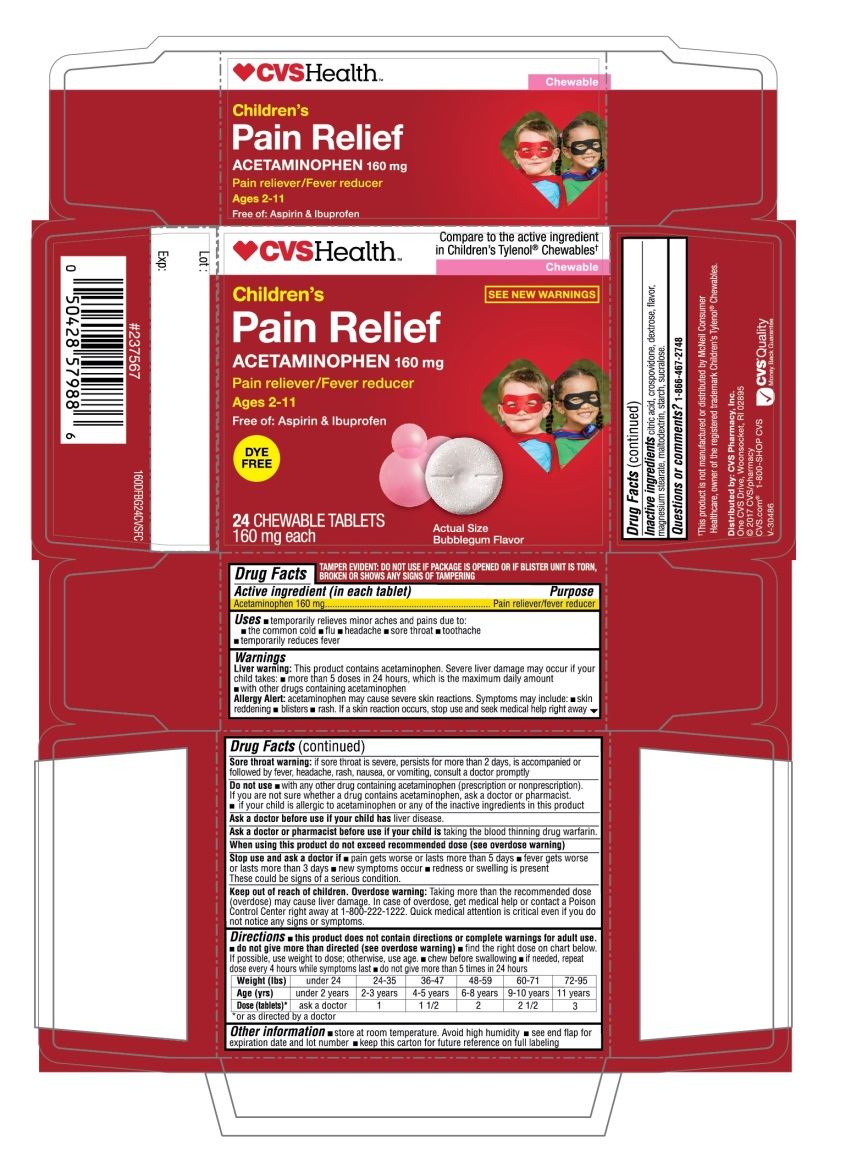 DRUG LABEL: Childrens Pain Relief
NDC: 69842-160 | Form: TABLET, CHEWABLE
Manufacturer: CVS Pharmacy,Inc.
Category: otc | Type: HUMAN OTC DRUG LABEL
Date: 20251208

ACTIVE INGREDIENTS: ACETAMINOPHEN 160 mg/1 1
INACTIVE INGREDIENTS: CITRIC ACID MONOHYDRATE; CROSPOVIDONE (120 .MU.M); DEXTROSE, UNSPECIFIED FORM; MAGNESIUM STEARATE; MALTODEXTRIN; STARCH, CORN; SUCRALOSE

Children’s Pain Relief Acetaminophen 160mg Dye Free Bubblegum Flavor Chewable Tablets

Active ingredient (in each tablet)

Acetaminophen 160 mg

Purpose

Pain reliever/fever reducer

Uses

- temporarily relieves minor aches and pains due to:
  - the common cold
  - flu
  - headache
  - sore throat
  - toothache
- temporarily reduces fever

Warnings

Liver warning: This product contains acetaminophen. Severe liver damage may occur if your child takes:

- more than 5 doses in 24 hours, which is the maximum daily amount
- with other drugs containing acetaminophen.

Allergy alert: acetaminophen may cause severe skin reactions. Symptoms may include:

- skin reddening
- blisters
- rash

If a skin reaction occurs, stop use and seek medical help right away

Sore throat warning:If sore throat is severe, persists for more than 2 days, is accompanied or followed by fever, headache, rash, nausea, or vomiting, consult a doctor promptly

Do not use

- with any other drug containing acetaminophen (prescription or nonprescription). If you are not sure whether a drug contains acetaminophen, ask a doctor or pharmacist.
- if your child is allergic to acetaminophen or any of the inactive ingredients in this product.

Ask a doctor before use if your child has

liver disease.

Ask a doctor or pharmacist before use if your child is

taking the blood thinning drug warfarin.

When using this product

do not exceed recommended dose (see overdose warning)

Stop use and ask a doctor if

- pain gets worse or lasts more than 5 days
- fever gets worse or lasts more than 3 days
- new symptoms occur
- redness or swelling is present

These could be signs of a serious condition.

Keep out of reach of children.

Overdose warning:Taking more than the recommended dose (overdose) may cause liver damage. In case of overdose, get medical help or contact a Poison Control Center right away at 1-800-222-1222. Quick medical attention is critical even if you do not notice any signs or symptoms.

Directions

- this product does not contain directions or complete warnings for adult use.
- do not give more than directed (see overdose warning)
- find the right dose on chart below. If possible, use weight to dose; otherwise use age.
- chew before swallowing
- if needed, repeat dose every 4 hours while symptoms last
- do not give more than 5 times in 24 hours

Weight (lbs) | under 24 | 24-35 | 36-47 | 48-59 | 60-71 | 72-95
Age (yrs) | under 2 years | 2-3- years | 4-5 years | 6-8 years | 9-10 years | 11 years
Dose(tablets)* | ask a doctor | 1 | 1 1/2 | 2 | 2 1/2 | 3

- *or as directed by a doctor

Other information

- store at room temperature Avoid high humidity.
- see end flap for expiration date and lot number
- keep this carton for future reference on full labeling

Inactive ingredients

citric acid, crospovidone, dextrose, flavor, magnesium stearate, maltodextrin, starch, sucralose

Questions or comments?

1-866-467-2748

Principal Display Panel

NDC 69842-160-24

Compare to the active ingredient in Children’s Tylenol®Chewables†

Children’s

Pain Relief

Acetaminophen 160 mg

Pain reliever/Fever reducer

Ages 2-11

Free of: Aspirin & Ibuprofen

BUBBLEGUM FLAVOR

24 CHEWABLE TABLETS

160 mg each

TAMPER EVIDENT: DO NOT USE IF PACKAGE IS OPENED OR IF BLISTER UNIT IS TORN, BROKEN OR SHOWS ANY SIGNS OF TAMPERING

†This product is not manufactured or distributed by McNeil Consumer Healthcare, owner of the registered trademark Children’s Tylenol®Chewables.

Distributed by: CVS Pharmacy, Inc,

One CVS Drive, Woonsocket, RI 02895

©2017 CVS/Pharmacy

CVS.com 1-800-SHOP CVS